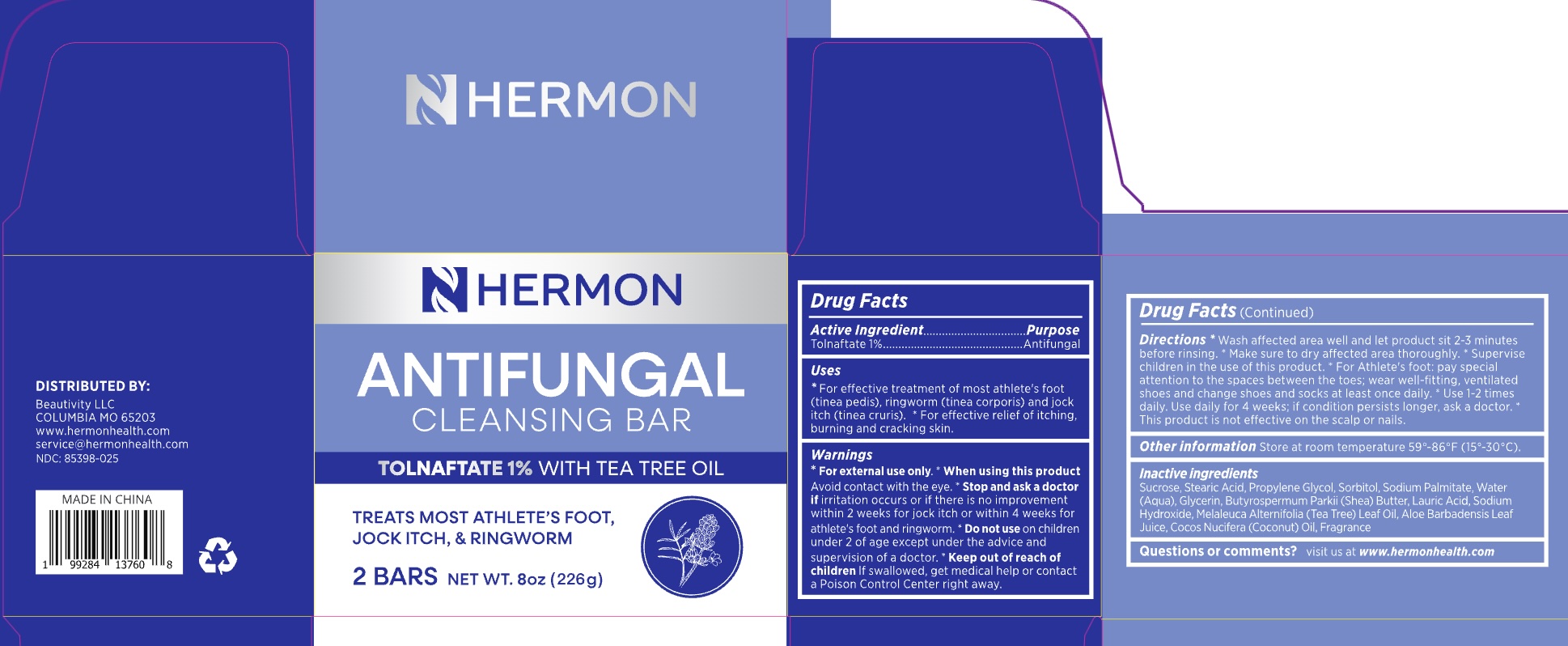 DRUG LABEL: Hermon Antifungal .soap.
NDC: 85398-025 | Form: SOAP
Manufacturer: Beautivity LLC
Category: otc | Type: HUMAN OTC DRUG LABEL
Date: 20260117

ACTIVE INGREDIENTS: TOLNAFTATE 10 mg/1 g
INACTIVE INGREDIENTS: AQUA; MELALEUCA ALTERNIFOLIA (TEA TREE) LEAF OIL; SORBITOL; COCOS NUCIFERA (COCONUT) OIL; PROPYLENE GLYCOL; GLYCERIN; STEARIC ACID; SODIUM HYDROXIDE; LAURIC ACID; SODIUM GLUTAMATE; BUTYROSPERMUM PARKII (SHEA) BUTTER; ALOE BARBADENSIS LEAF JUICE; SUCROSE; SODIUM PALMITATE

85398-025-updated

ACTIVE INGREDIENT

Tolnaftate 1%

PURPOSE

Antifungal

DOSAGE AND ADMINISTRATION

- For effective treatment of most athlete’s foot (tinea pedis), ringworm (tinea corporis) and jock itch (tinea cruris).
- For effective relief of itching, burning and cracking skin.

INDICATIONS AND USAGE

- Wash affected area well and let product sit 2–3 minutes before rinsing.
- Make sure to dry affected area thoroughly.
- Supervise children in the use of this product.
- For Athlete’s foot: pay special attention to the spaces between the toes; wear well-fitting, ventilated shoes and change shoes and socks at least once daily.
- Use 1–2 times daily. Use daily for 4 weeks; if condition persists longer, ask a doctor.
- This product is not effective on the scalp or nails.

WARNINGS

For external use only.

DO NOT USE

on children under 2 years of age unless directed bya doctor.

WHEN USING

avoide contact with eyes, If contact occurs, rinse thoroughly with water.

STOP USE

Stop and ask a doctor if irritation occurs or if there is no improvement within 2 weeks for jock itch or within 4 weeks for athlete’s foot and ringworm.

KEEP OUT OF REACH OF CHILDREN

If swallowed,get medical helpor contact a Poison Control Center right away.

INACTIVE INGREDIENT

Sucrose, Stearic Acid, Propylene Glycol, Sorbitol, Sodium Palmitate, Water (Aqua), Glycerin, Butyrospermum Parkii (Shea) Butter, Lauric Acid, Sodium Hydroxide, Melaleuca Alternifolia (Tea Tree) Leaf Oil, Aloe Barbadensis Leaf Juice, Cocos Nucifera (Coconut) Oil, Fragrance

OTHER SAFETY INFORMATION

Store at room temperature 59°–86°F (15°–30°C).

QUESTIONS

visit us at www.hermonhealth.com